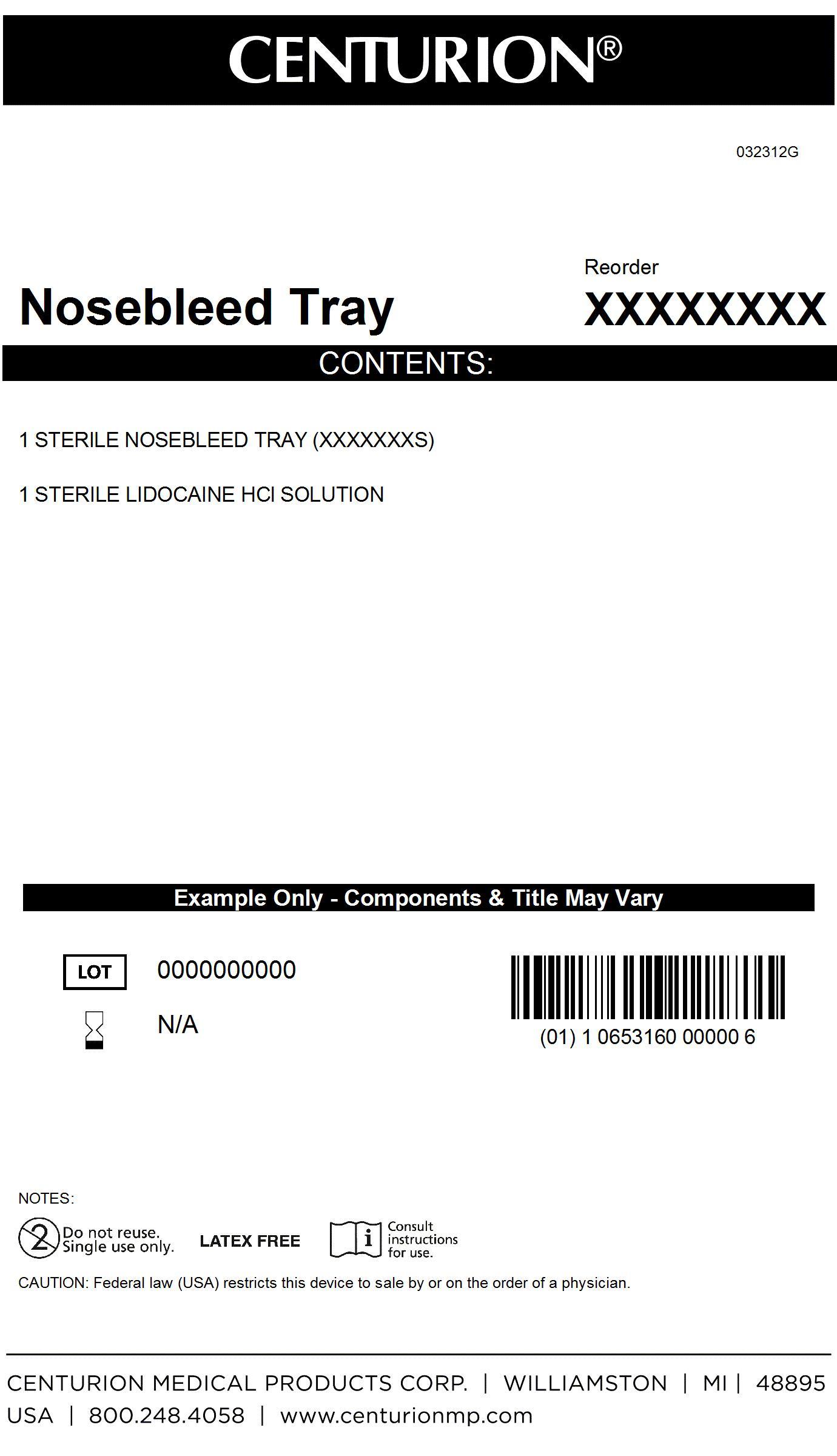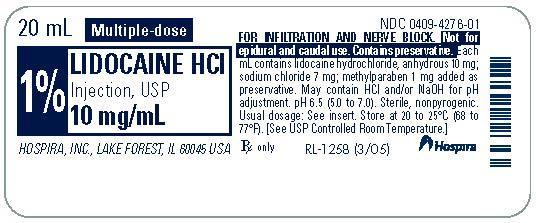 DRUG LABEL: ENT Kit
NDC: 24840-1308 | Form: KIT | Route: INFILTRATION
Manufacturer: Centurion Medical Products
Category: other | Type: MEDICAL DEVICE
Date: 20131001

ACTIVE INGREDIENTS: LIDOCAINE HYDROCHLORIDE ANHYDROUS 10 mg/1 mL
INACTIVE INGREDIENTS: SODIUM CHLORIDE 7 mg/1 mL; Water; SODIUM HYDROXIDE; HYDROCHLORIC ACID

ENT Kit

DESCRIPTION

AQUEOUS SOLUTIONS FOR INFILTRATION

AND NERVE BLOCK

Ampul

Plastic Multiple-Dose Fliptop Vial

Glass Teartop Vial

Rx only